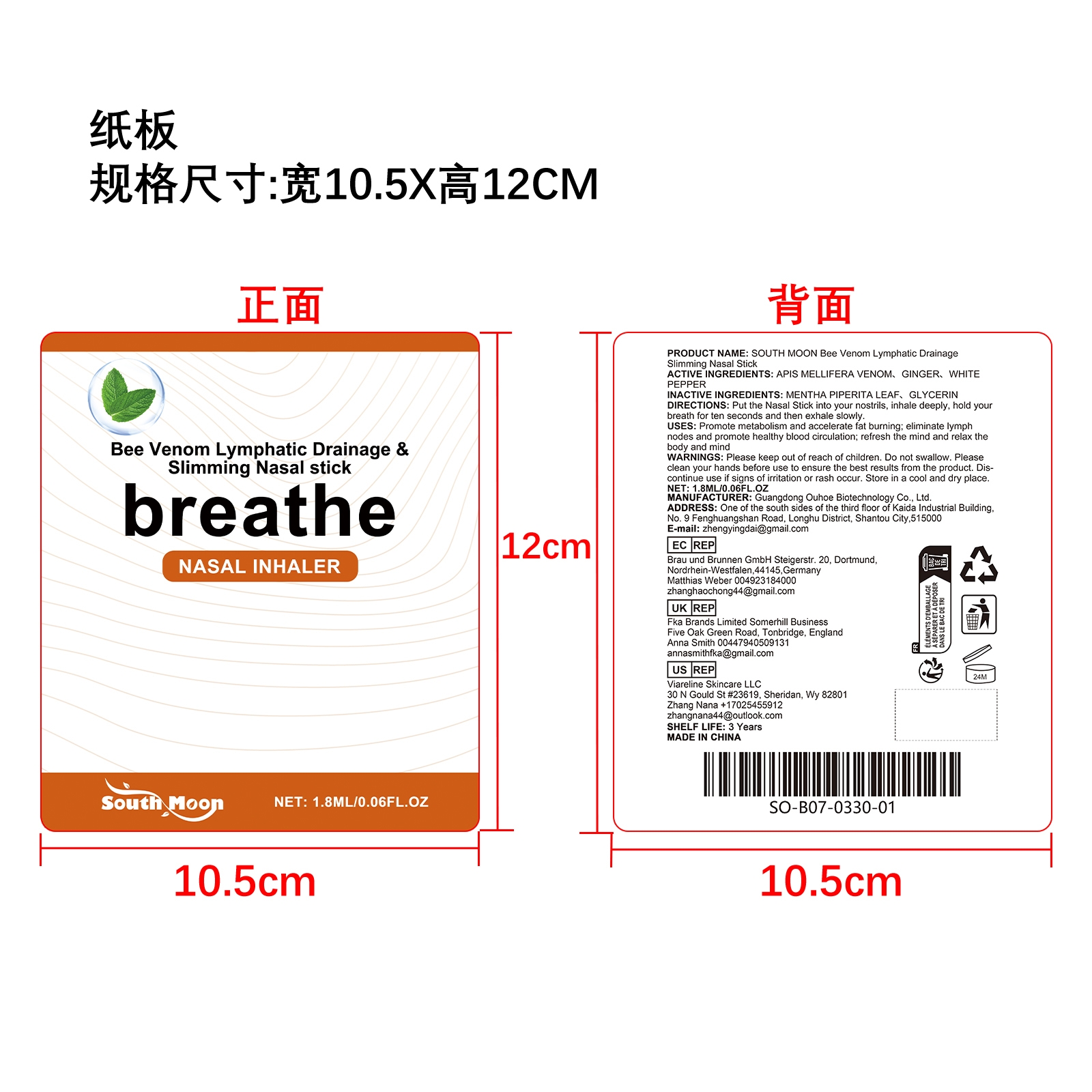 DRUG LABEL: SOUTH MOON Bee Venom Lymphatic Drainage Slimming Nasal Stick
NDC: 84744-066 | Form: LIQUID
Manufacturer: Guangdong Ouhoe Biotechnology Co., Ltd.
Category: otc | Type: HUMAN OTC DRUG LABEL
Date: 20241028

ACTIVE INGREDIENTS: GINGER 0.18 mg/1.8 mg; APIS MELLIFERA VENOM 0.54 mg/1.8 mg; WHITE PEPPER 0.27 mg/1.8 mg
INACTIVE INGREDIENTS: GLYCERIN 0.54 mg/1.8 mg; MENTHA PIPERITA LEAF 0.27 mg/1.8 mg

ACTIVE INGREDIENTS

APIS MELLIFERA VENOM、 GINGER、WHITE PEPPER

PURPOSE

Promote metabolism and accelerate fat burning; eliminate lymph nodes and promote healthy blood circulation; refresh the mind and relax the body and mind.

USE

Put the Nasal Stick into your nostrils, inhale deeply, hold your breath for ten seconds and then exhale slowly.

WARNINGS

Please keep out of reach of children. Do not swallow. Please clean your hands before use to ensure the best results from the product. Discontinue use if signs of irritation or rash occur. Store in a cool and dry place.

STOP USE

Discontinue use if signs of irritation or rash occur.

DO NOT USE

Discontinue use if signs of irritation or rash occur.

KEEP OUT OF REACH OF CHILDREN

Please keep out of reach of children. Do not swallow.

STORAGE AND HANDLING

Store in a cool and dry place.

INACTIVE INGREDIENT

MENTHA PIPERITA LEAF、GLYCERIN